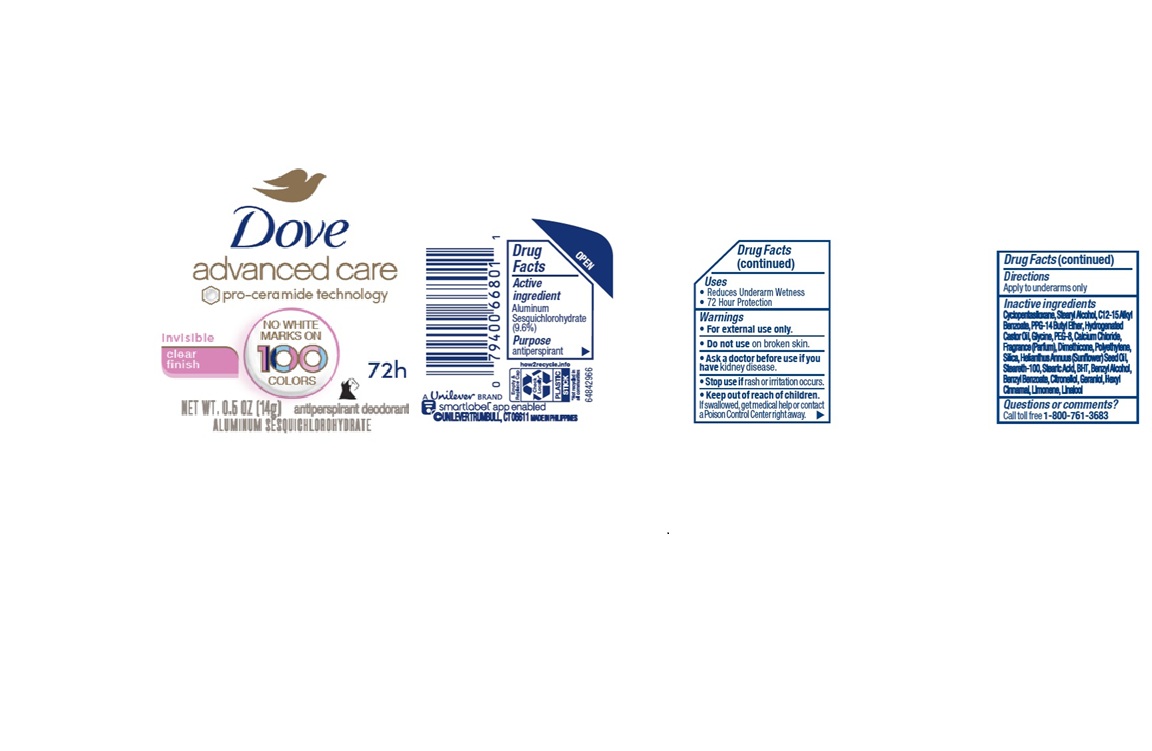 DRUG LABEL: Dove
NDC: 64942-2400 | Form: STICK
Manufacturer: Conopco d/b/a Unilever
Category: otc | Type: HUMAN OTC DRUG LABEL
Date: 20251104

ACTIVE INGREDIENTS: ALUMINUM SESQUICHLOROHYDRATE 9.6 g/100 g
INACTIVE INGREDIENTS: PPG-14 BUTYL ETHER; BHT; HYDROGENATED CASTOR OIL; C12-15 ALKYL BENZOATE; POLYETHYLENE; BENZYL ALCOHOL; BENZYL BENZOATE; HELIANTHUS ANNUUS (SUNFLOWER) SEED OIL; STEARYL ALCOHOL; GLYCINE; CYCLOPENTASILOXANE; CITRONELLOL; GERANIOL; HEXYL CINNAMAL; PEG-8; LINALOOL; SILICA; CALCIUM CHLORIDE; DIMETHICONE; STEARETH-100; LIMONENE, (+/-)-

Dove Advanced Care Invisible Clear Finish 72H Antiperspirant Deodorant

DESCRIPTION

Dove Advanced Care Invisible Clear Finish 72H Antiperspirant Deodorant

ACTIVE INGREDIENT

Aluminum Sesquichlorohydrate 9.6%

PURPOSE

antiperspirant

INDICATIONS AND USAGE

reduces underarm wetness

72 Hour Protection

WARNINGS

• For external use only.

• Do not use on broken skin.

• Ask a doctor before use if you have kidney disease.

• Stop use if rash or irritation occurs.

Keep out of reach of children.

If swallowed, get medical help or contact a Poison Control Center right away.

DOSAGE AND ADMINISTRATION

Apply to underarms only

INACTIVE INGREDIENT

Cyclopentasiloxane, Stearyl Alcohol, C12-15 Alkyl Benzoate, PPG-14 Butyl Ether, Hydrogenated Castor Oil, Glycine, PEG-8, Calcium Chloride, Fragrance (Parfum), Dimethicone, Polyethylene, Silica, Helianthus Annuus (Sunflower) Seed Oil, Steareth-100, Stearic Acid, BHT, Benzyl Alcohol, Benzyl Benzoate, Citronellol, Geraniol, Hexyl Cinnamal, Limonene, Linalool

QUESTIONS

Call toll-free 1-800-761-3683